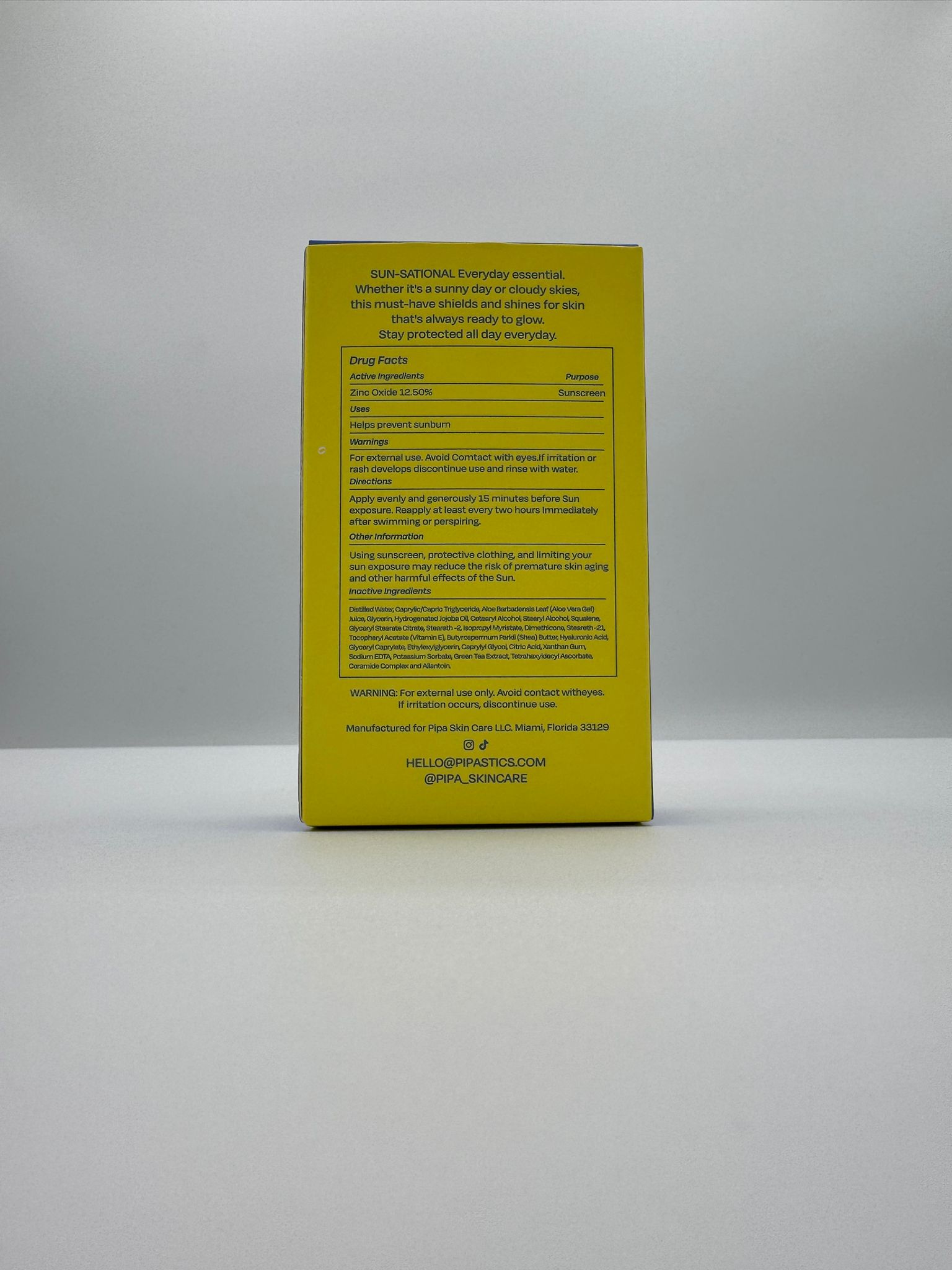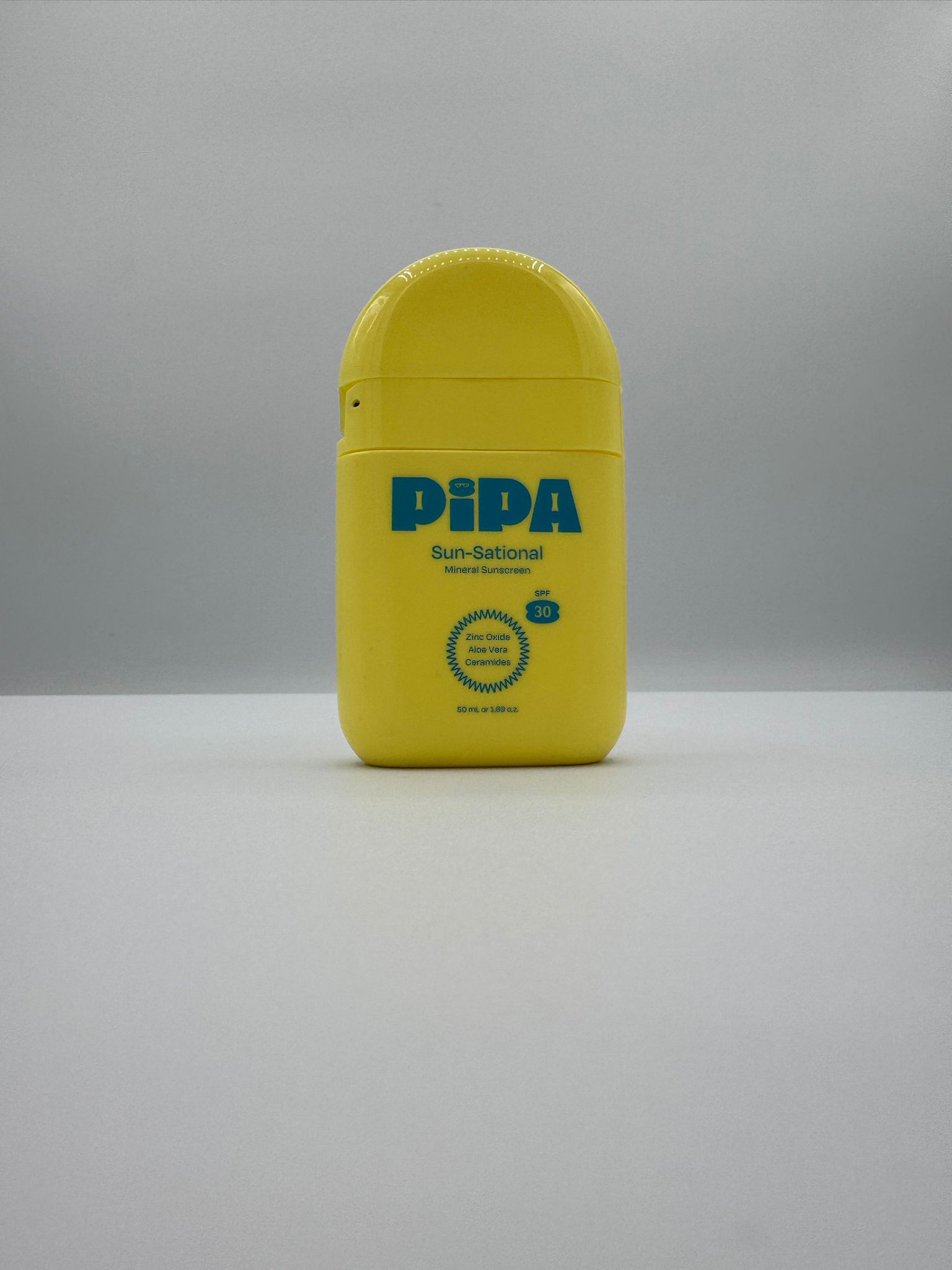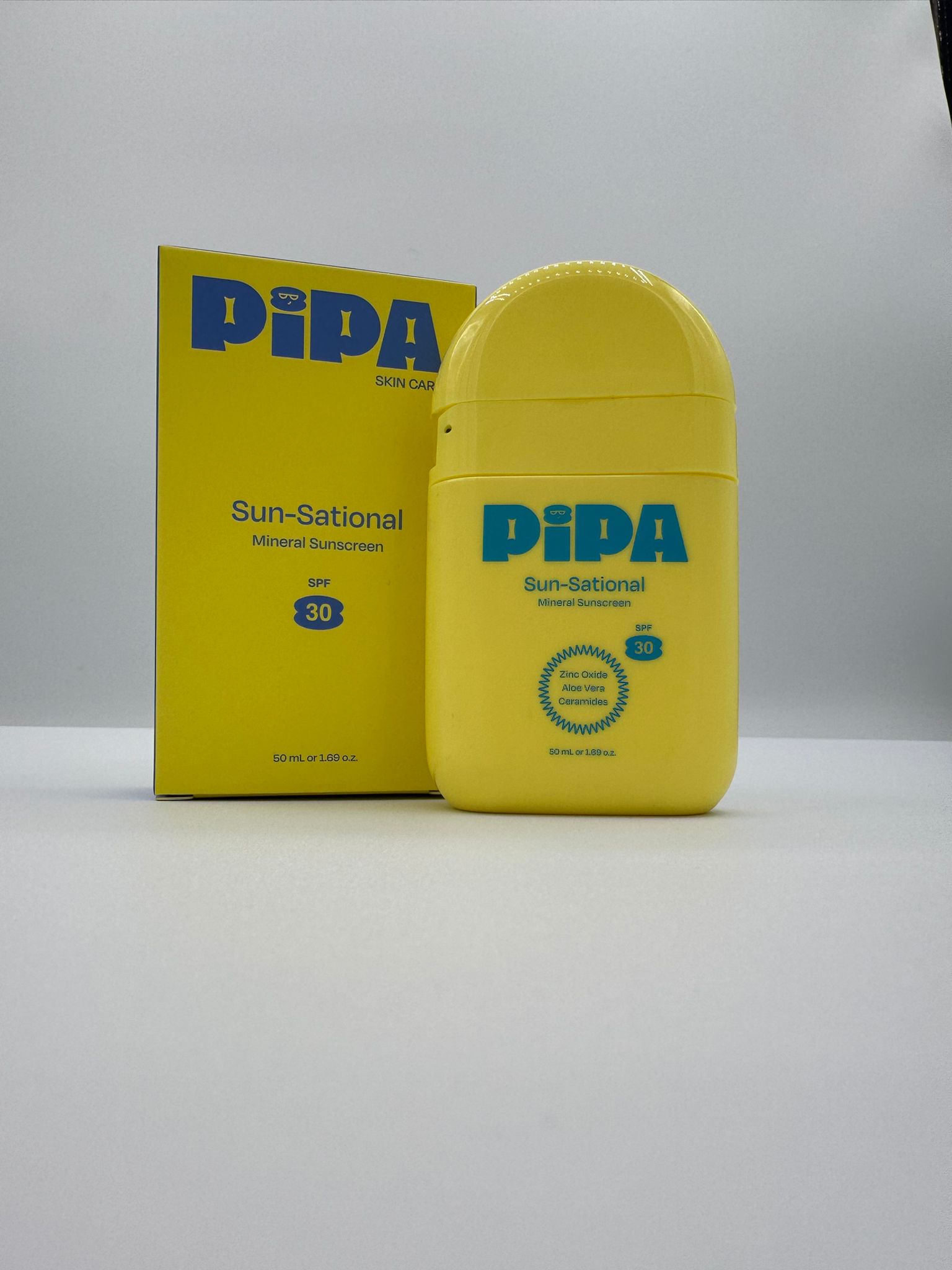 DRUG LABEL: PIPA SKIN CARE SUN-SATIONAL
NDC: 84178-002 | Form: CREAM
Manufacturer: EVI LABS
Category: otc | Type: HUMAN OTC DRUG LABEL
Date: 20260108

ACTIVE INGREDIENTS: ZINC OXIDE 6.25 g/50 g
INACTIVE INGREDIENTS: CAPRYLYL GLYCOL 0.1 g/50 g; ALOE VERA LEAF 5 g/50 g; GLYCERYL CAPRYLATE 0.3 g/50 g; CETEARYL ALCOHOL 1.75 g/50 g; POTASSIUM SORBATE 0.15 g/50 g; ISOEICOSANE 0.75 g/50 g; STEARETH-21 0.15 g/50 g; ETHYLHEXYLGLYCERIN 0.15 g/50 g; GREEN TEA LEAF 0.11 g/50 g; CAPRYLIC/CAPRIC TRIGLYCERIDE 1.25 g/50 g; ALLANTOIN 0.1 g/50 g; TETRAHEXYLDECYL ASCORBATE 0.25 g/50 g; HYDROGENATED JOJOBA OIL 1 g/50 g; SORBITOL 1.25 g/50 g; STEARYL ALCOHOL 0.75 g/50 g; STEARETH-2 0.3 g/50 g; BUTYROSPERMUM PARKII (SHEA) BUTTER 0.25 g/50 g; ANHYDROUS CITRIC ACID 0.08 g/50 g; XANTHAN GUM 0.1 g/50 g; GLYCERIN 5 g/50 g; WATER 19.36 g/50 g; CERAMIDE 1 0.3 g/50 g; DIMETHICONE 1 g/50 g; ISOPROPYL MYRISTATE 0.5 g/50 g; GLYCERYL STEARATE CITRATE 0.75 g/50 g; SQUALANE 0.75 g/50 g; HYALURONIC ACID 0.2 g/50 g; EDETATE SODIUM 0.1 g/50 g; PROPYLENE GLYCOL 1.25 g/50 g; ALPHA-TOCOPHEROL 0.75 g/50 g

PIPA SKIN CARE -SUN SATIONAL

Active Ingredients

Zinc Oxide 12.50%

Purpose

Sunscreen

USES

Helps prevent sunburn

Warnings

For external use. Avoid contact with eyes. If irritation or rash develops discontinue use and rinse with water.

Directions

Apply evenly and generously 15 minutes before Sun exposure. Reapply at least every two hours immediately after swimming or perspiring.

Administration

For external use.

Keep out of reach of children's

Keep out of the reach of children. If swallowed get medical help or contact a poison control center immediately.

Inactive Ingredients

Distilled water, Caprylic/capric Triglyceride, Aloe Barbadensis Leaf (Aloe Vera Gel) Juice, Glycerin, Hydrogenated Jojoba Oil, Cetearyl Alcohol, Stearyl Alcohol, Squalene, Glyceryl Stearate Citrate, Steareth-2, Isopropyl Myristate, Stearaeth-21, Dimethicone, Tocopheryl Acetate (Vitamin E), Butyrospermum Parki (Shea) Butter, Hyaluronic Acid, Glyceryl Caprylate, Ethylexylglycerin, Caprylyl Glyco, Citric Acid, Xanthan Gum, Sodium EDTA, Potassium Sorbate, Green Tea Extract, Tetrahexyldecyl Ascorbate, Ceramide Complex and Allantoin.

Principal Display Panel

Panel Drug Fast